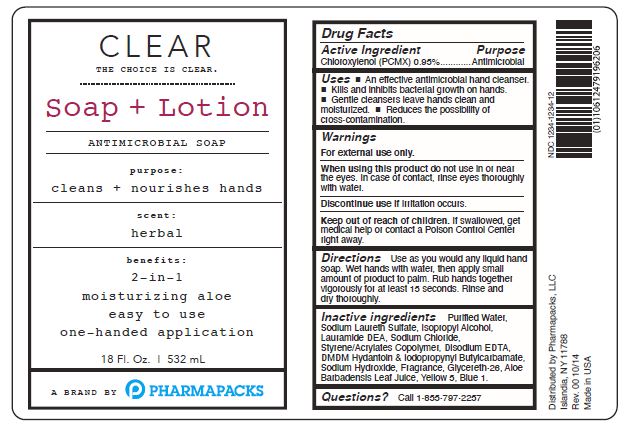 DRUG LABEL: CLEAR S plus L
NDC: 73599-001 | Form: LIQUID
Manufacturer: PHARMAPACKS, LLC
Category: otc | Type: HUMAN OTC DRUG LABEL
Date: 20200305

ACTIVE INGREDIENTS: CHLOROXYLENOL 0.95 g/100 mL
INACTIVE INGREDIENTS: EDETATE DISODIUM ANHYDROUS; DMDM HYDANTOIN; IODOPROPYNYL BUTYLCARBAMATE; SODIUM LAURETH SULFATE; ISOPROPYL ALCOHOL; SODIUM CHLORIDE; FD&C YELLOW NO. 5; FD&C BLUE NO. 1; WATER; LAURIC DIETHANOLAMIDE; STYRENE/ACRYLAMIDE COPOLYMER (MW 500000); SODIUM HYDROXIDE; ALOE VERA LEAF; GLYCERETH-26

Active Ingredient

Choroxylenol (PCMX) 0.95%

Purpose

Antimicrobial

Uses

- An effective antimicrobial hand cleanser.
- Kills and inhibits bacterial growth on hands.
- Gentle cleansers leave hands clean and misturized.
- Reduces the possibility of cross contamination.

Warnings

For external use only.

When using this product do not use in or near the eyes.

In case of contact, rinse eyes thoroughly with water.

Discontinue use if irritation occurs.

Keep out of reach of children.

If swallowed, get medical help or contact a Poison Control Center right away.

Directions

Use as you would any liquid hand soap.

Wet hands with water, then apply small amounts of product to palm.

Rub hands together vigorously for at least 15 seconds.

Rinse and dry thoroughly.

Inactive ingredients

Purified Water, Sodium Laureth Sulfate, Isopropyl Alcohol, Lauramine DEA, Sodium Chloride, Styrene/Acrylates Copolymer, Disodium EDTA, DMDM Hydantoin and Iodopropynyl Butylcarbamate,, Sodium Hydroxide, Fragrance, Glycereth-26, Aloe Barbadensis Leaf Juice, Yellow 5, Blue 1.

Questions?

Call 1-855-797-2257

PACKAGE LABEL

CLEAR

The Choice Is Clear

SOAP + Lotion

Antimicrobial Soap

purpose:

cleans + nourishes hands

scent:

herbal

benefits:

2-in-1

moisturizing aloe

easy to use

one-handed application

18 Fl. Oz. 532 mL

A Brand By PHARMAPACKS